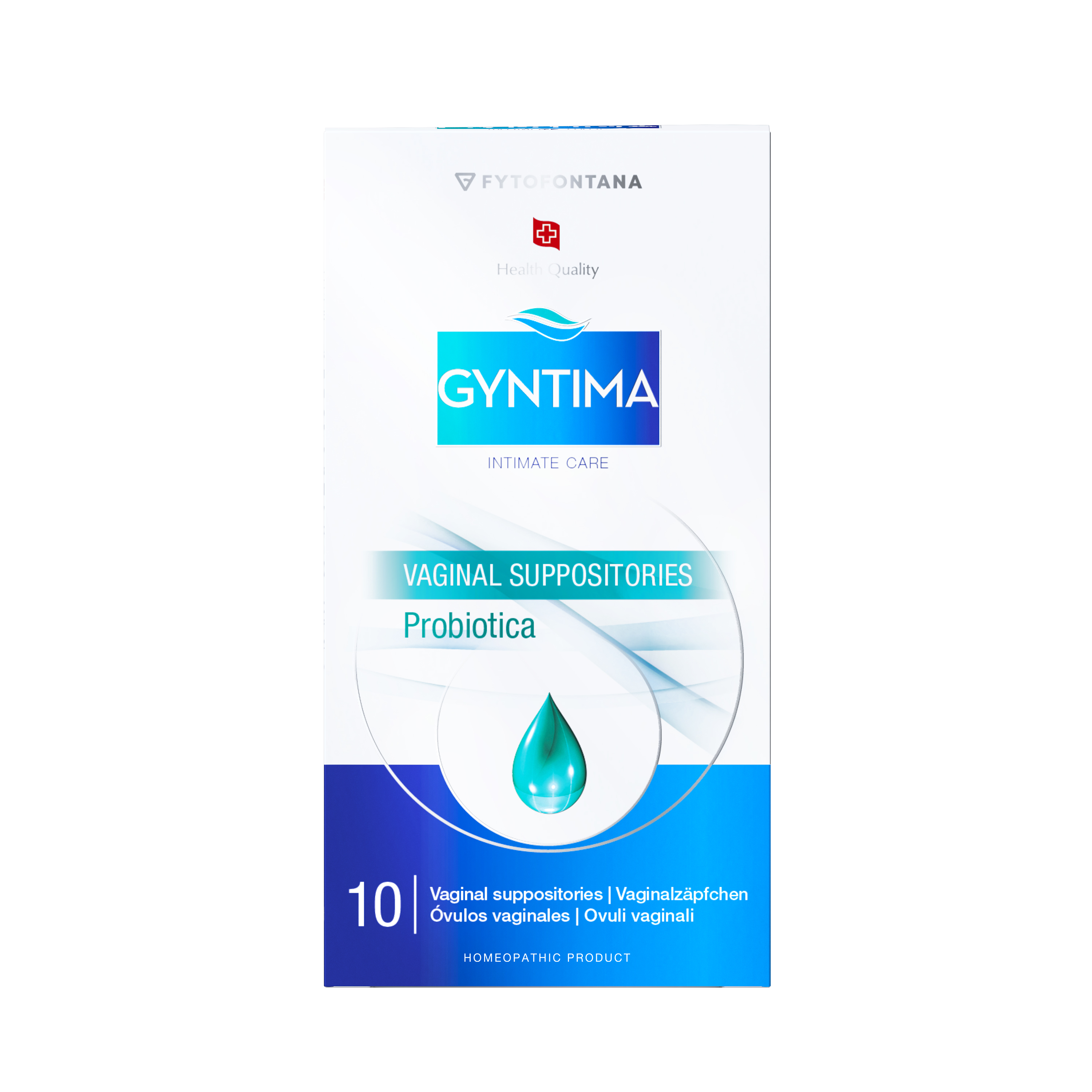 DRUG LABEL: GYNTIMA Probiotica
NDC: 85401-020 | Form: SUPPOSITORY
Manufacturer: Fytofontana LLC
Category: homeopathic | Type: HUMAN OTC DRUG LABEL
Date: 20250401

ACTIVE INGREDIENTS: LACTIC ACID, DL- 2 [hp_X]/1 1; SAGE 3 [hp_X]/1 1; FOLIC ACID 4 [hp_X]/1 1
INACTIVE INGREDIENTS: HYDROLYZED CASEIN (ENZYMATIC; 1000 MW); PEG-32; MAGNESIUM SULFATE; SODIUM CHLORIDE; LACTOSE MONOHYDRATE; POLYSORBATE 20; PEG-20

Active Ingredients (per suppository, HPUS):

Acidum folicum 4X HPUS – Supports tissue health and repair

Acidum lacticum 2X HPUS – Supports vaginal pH balance

Extractum Salviae officinalis 3X HPUS – Traditionally used for soothing support

Magnesii sulphas 2X HPUS – Supports hydration and relief from irritation

Purpuse

Purpose:

Acidum folicum – Supports tissue health and repair.

Acidum lacticum – Supports vaginal pH balance.

Extractum Salviae officinalis – Provides soothing support.

Magnesii sulphas – Supports hydration and relief from irritation.

Uses:

Helps maintain the natural balance of the vaginal microbiome.

Helps relieve discomfort, irritation, and pH imbalance.

Supports the vaginal flora balance after antibiotic treatments.

Designed to promote vaginal wellness by supporting the natural environment for beneficial bacteria to thrive.

INDICATIONS AND USAGE

Women seeking preventive intimate care, particularly after:

• Antibiotic or disinfectant use

• Swimming, sexual activity, or other microbiome disturbances

• Occasional mild discomfort or irritation not requiring pharmaceutical treatment

Inactive Ingredients

PEG 32, Lactosum, Polysorbate 20, PEG 20, Natrii Chloridum, Proteose Pepton

INSTRUCTIONS FOR USE

Wash hands and intimate area thoroughly.

Remove the suppository from the blister pack.

Insert deeply into the vagina, preferably in the evening before bed.

Use a sanitary pad, as minor discharge will occur.

These uses are based on traditional homeopathic practice. They have not been reviewed by the Food and Drug Administration.

Warnings

Do not use during menstruation.

Do not use during pregnancy.

The vaginal suppository is intended for vaginal use only.

Do not use if the packaging appears damaged.

Do not use after the expiration date indicated on the package.

Keep out of the reach of small children.

The active ingredients in this product are prepared in accordance with the Homeopathic Pharmacopoeia of the United States (HPUS). These uses are based on traditional homeopathic practice. They have not been reviewed by the Food and Drug Administration.

KEEP OUT OF REACH OF CHILDREN

Keep out of the reach of children. In case of accidental ingestion, seek medical help or contact a Poison Control Center right away.

Precautions

Consult your gynecologist when using vaginal preparations along with vaginal contraceptives.

If problems still persist after several days of use, consult your gynecologist.

After gynecological procedures, use only with a physician’s approval.

Any possible discoloration is due to natural plant substances in the product and is not a sign that the preparation is defective.

STORAGE AND HANDLING

Store in a cool, dry place away from heat sources and direct sunlight.
Shelf life: 36 months from the date of manufacture.

Distributed by:
Fytofontana LLC
382 NE 191st St PMB 850628
Miami, Florida 33179-3899 USA

Manufacturer:
Herb-Pharma Corporation s.r.o., 935 65 Veľké Ludince, Slovakia
Under license from Herb-Pharma AG Schweiz, Waldmannstrasse 6, 8001 Zürich, Switzerland

For more information, visit:
www.fytofontana.com

Directions:

Wash hands and intimate area thoroughly.

Remove one suppository from the blister pack.

Insert deeply into the vagina, preferably in the evening before bed.

Use a sanitary pad as minor discharge may occur.

Dosage & Use:

• Treatment: 1 suppository daily for 10 consecutive days

• Prevention: 1–2 suppositories per week, long-term maintenance